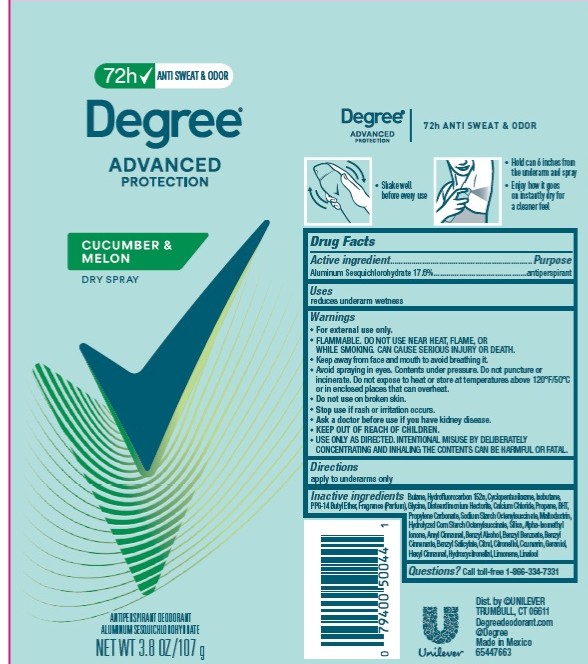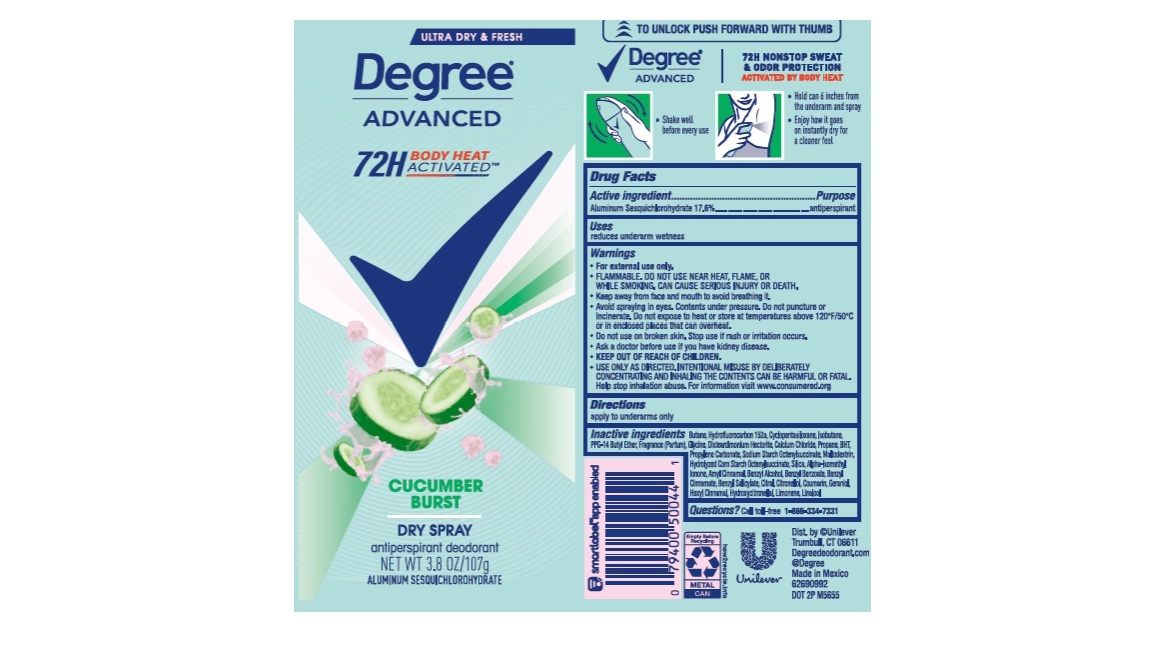 DRUG LABEL: Degree
NDC: 64942-2225 | Form: AEROSOL, SPRAY
Manufacturer: Conopco, Inc. d/b/a Unilever
Category: otc | Type: HUMAN OTC DRUG LABEL
Date: 20260212

ACTIVE INGREDIENTS: ALUMINUM SESQUICHLOROHYDRATE 17.6 g/100 g
INACTIVE INGREDIENTS: BENZYL BENZOATE; BENZYL CINNAMATE; COUMARIN; HYDROXYCITRONELLAL; LINALOOL, (+/-)-; BENZYL SALICYLATE; BENZYL ALCOHOL; CITRAL; SILICON DIOXIDE; MALTODEXTRIN; PROPYLENE CARBONATE; GLYCINE; LIMONENE, (+)-; ISOBUTANE; .BETA.-CITRONELLOL, (R)-; BUTANE; 1,1-DIFLUOROETHANE; CYCLOMETHICONE 5; PPG-14 BUTYL ETHER; DISTEARDIMONIUM HECTORITE; CALCIUM CHLORIDE; PROPANE; BUTYLATED HYDROXYTOLUENE; ISOMETHYL-.ALPHA.-IONONE; .ALPHA.-HEXYLCINNAMALDEHYDE; GERANIOL; .ALPHA.-AMYLCINNAMALDEHYDE

Degree Advanced Cucumber Burst Dry Spray 72H Antiperspirant Deodorant

Drug Facts

Active ingredient

Aluminum Sesquichlorohydrate (17.6%)

Purpose

antiperspirant

Uses

reduces underarm wetness

Directions

For underarms use only

Inactive ingredients

Butane, Hydrofluorocarbon 152a, Cyclopentasiloxane, Isobutane, PPG-14 Butyl Ether, Fragrance (Parfum), Glycine, Disteardimonium Hectorite, Calcium Chloride, Propane, BHT, Propylene Carbonate, Sodium Starch Octenylsuccinate, Maltodextrin, Hydrolyzed Corn Starch Octenylsuccinate, Silica, Alpha-Isomethyl Ionone, Amyl Cinnamal, Benzyl Alcohol, Benzyl Benzoate, Benzyl Cinnamate, Benzyl Salicylate, Citral, Citronellol, Coumarin,Geraniol , Hexyl Cinnamal, Hydrocitronellal, Limonene, Linalool

Questions?

Call toll-free 1-866-334-7331